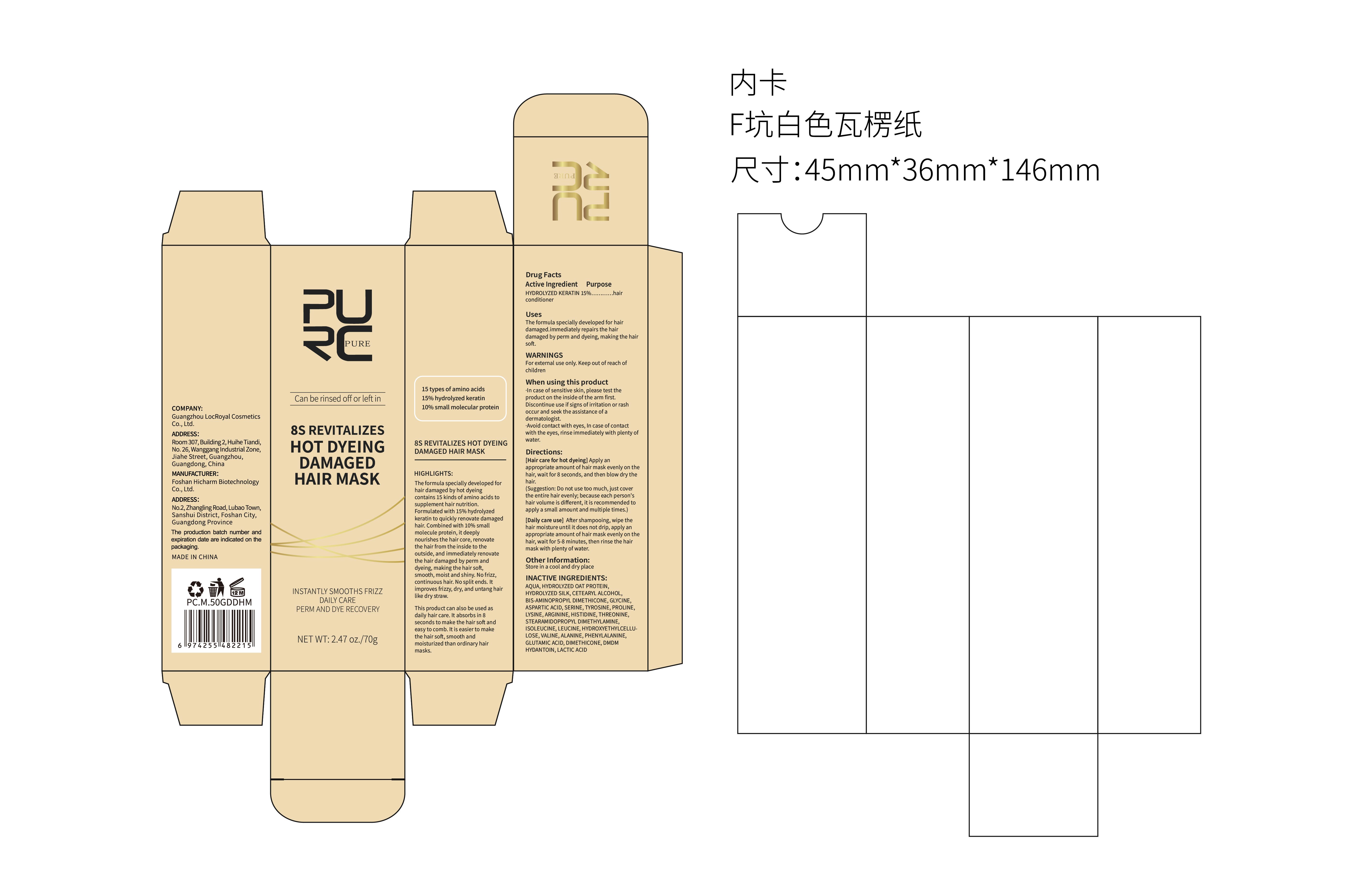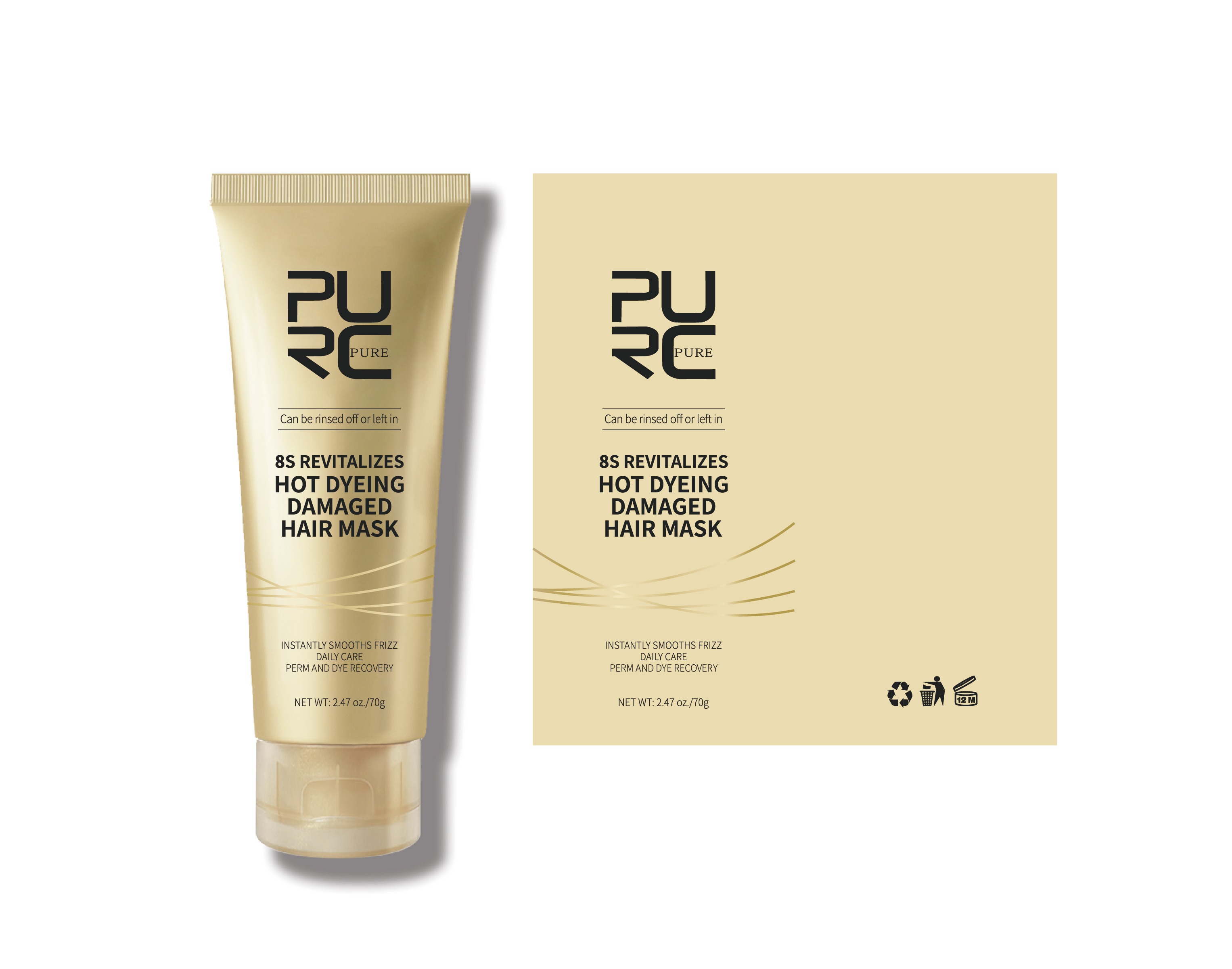 DRUG LABEL: PURC 8S REVITALIZES HOT DYEING DAMAGED HAIR MASK
NDC: 84186-003 | Form: CREAM
Manufacturer: Guangzhou Bonnieco Cosmetics Co., Ltd
Category: otc | Type: HUMAN OTC DRUG LABEL
Date: 20240319

ACTIVE INGREDIENTS: COCODIMONIUM HYDROXYPROPYL HYDROLYZED KERATIN (1000 MW) 15 g/100 g
INACTIVE INGREDIENTS: PROLINE; HISTIDINE; DIMETHICONE; GLYCINE; TYROSINE; ISOLEUCINE; STEARAMIDOPROPYL DIMETHYLAMINE; GLUTAMIC ACID; LYSINE; THREONINE; PHENYLALANINE; LACTIC ACID; AMINOPROPYL DIMETHICONE (1000 MPA.S); DMDM HYDANTOIN; WATER; HYDROLYZED SOY PROTEIN (ENZYMATIC; 2000 MW); CETOSTEARYL ALCOHOL; ARGININE; LEUCINE; VALINE; HYDROXYETHYL CELLULOSE, UNSPECIFIED; ALANINE; HYDROLYZED BOVINE ELASTIN (BASE; 1000 MW); ASPARTIC ACID; SERINE

84186-003

Active Ingredient

HYDROLYZED KERATIN 15%

Purpose

The formula specially developed for hair damaged.immediately repairs the hair damaged by perm and dyeing, making the hair soft.

Use

Squeeze out and apply gently to hair

Warnings

For external use only. Keep out of reach of children

When Using

·In case of sensitive skin, please test the product on the inside of the arm first. Discontinue use if signs of irritation or rash occur and seek the assistance of a dermatologist.
·Avoid contact with eyes, In case of contact with the eyes, rinse immediately with plenty of water.

Keep Oot Of Reach Of Children

If swallowed, get medical help or contact a poison control center right away.

Directions

[Hair care for hot dyeing] Apply an appropriate amount of hair mask evenly on the hair, wait for 8 seconds, and then blow dry the hair.
(Suggestion: Do not use too much, just cover the entire hair evenly; because each person's hair volume is different, it is recommended to apply a small amount and multiple times.)
[Daily care use] After shampooing, wipe the hair moisture until it does not drip, apply an appropriate amount of hair mask evenly on the hair, wait for 5-8 minutes, then rinse the hair mask with plenty of water.

Other information

The formula specially developed for hair damaged by hot dyeing contains 15 kinds of amino acids to supplement hair nutrition. Formulated with 15% hydrolyzed keratin to quickly renovate damaged hair. Combined with 10% small molecule protein, it deeply nourishes the hair core, renovate the hair from the inside to the outside, and immediately renovate the hair damaged by perm and dyeing, making the hair soft, smooth, moist and shiny. No frizz, continuous hair. No split ends. It improves frizzy, dry, and untang hair like dry straw.
This product can also be used as daily hair care. It absorbs in 8 seconds to make the hair soft and easy to comb. It is easier to make the hair soft, smooth and moisturized than ordinary hair masks.

Can be rinsed off or left in

15 types of amino acids
15% hydrolyzed keratin
10% small molecular protein

Inactive ingredients

AQUA, HYDROLYZED OAT PROTEIN, HYDROLYZED SILK, CETEARYL ALCOHOL, BIS-AMINOPROPYL DIMETHICONE, GLYCINE, ASPARTIC ACID, SERINE, TYROSINE, PROLINE, LYSINE, ARGININE, HISTIDINE, THREONINE, STEARAMIDOPROPYL DIMETHYLAMINE, ISOLEUCINE, LEUCINE, HYDROXYETHYLCELLULOSE, VALINE, ALANINE, PHENYLALANINE, GLUTAMIC ACID, DIMETHICONE, DMDM HYDANTOIN, LACTIC ACID